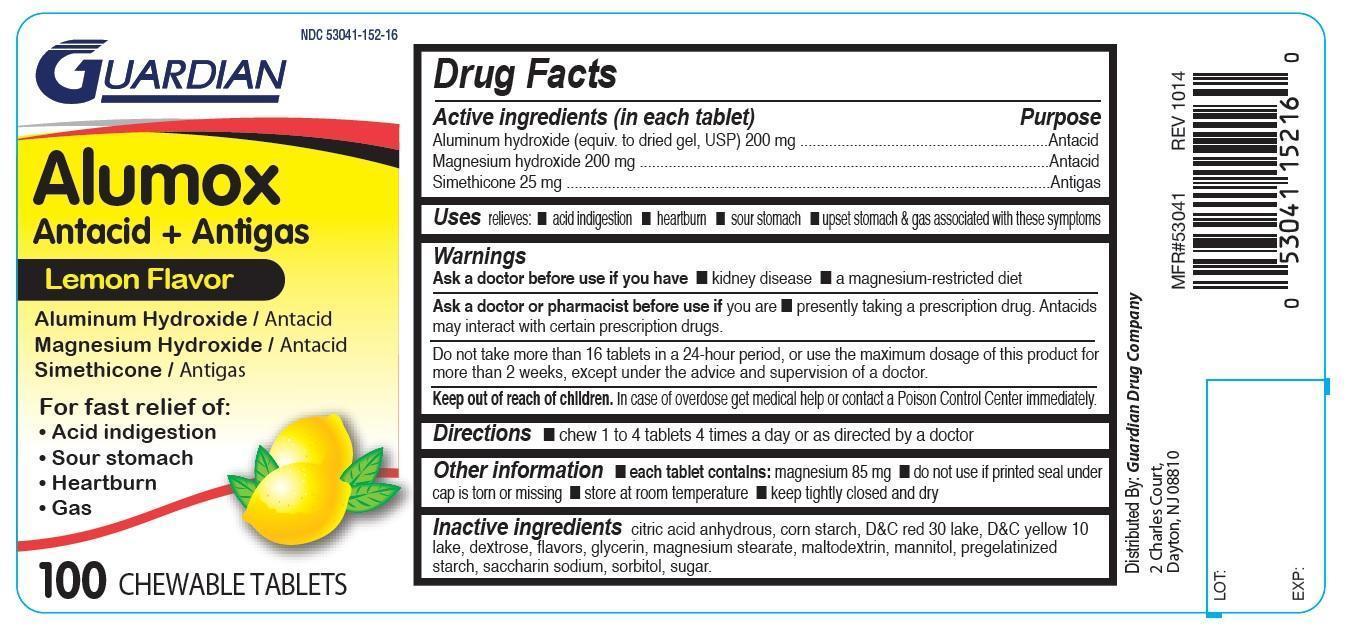 DRUG LABEL: Alumox
NDC: 53041-152 | Form: TABLET, CHEWABLE
Manufacturer: Guardian Drug Company
Category: otc | Type: HUMAN OTC DRUG LABEL
Date: 20200117

ACTIVE INGREDIENTS: ALUMINUM HYDROXIDE 200 mg/1 1; MAGNESIUM HYDROXIDE 200 mg/1 1; DIMETHICONE 25 mg/1 1
INACTIVE INGREDIENTS: ANHYDROUS CITRIC ACID; STARCH, CORN; D&C RED NO. 30; D&C YELLOW NO. 10; DEXTROSE; GLYCERIN; MAGNESIUM STEARATE; MALTODEXTRIN; MANNITOL; SACCHARIN SODIUM; SORBITOL; RAW SUGAR

Guardian Alumox Tablets

Active ingredients (in each tablet)

Aluminum hydroxide (equiv. to dried gel, USP) 200 mg

Magnesium hydroxide 200 mg

Simethicone 25 mg

Purpose

Antacid

Antacid

Antigas

Uses

relieves:

acid indigestion

heartburn

sour stomach

upset stomach & gas associated with these symptoms

Warnings

Ask a doctor before use if you have

- kidney disease
- a magnesium-restricted diet

Ask a doctor or pharmacist before use if you are

- presently taking a prescription drug. Antacids may interact with certain certain prescription drugs.

Do not take

more than 16 tablets in a 24-hour period, or use the maximum dosage of this product for more than 2 weeks, except under the advice and supervision of a doctor.

keep out of reach of children. In case of overdose get medical help or contact a poison control center immediately.

Directions

- chew 1 to 4 tablets 4 times a day or as directed by a doctor.

Other information

- each tablet contains: magnesium 85 mg
- do not use if seal under cap is torn or missing
- store at room temperature
- keep tightly closed and dry

Inactive ingredients

citric acid anhydrous, corn starch, D&C red 30 lake, D&C yellow 10 lake, dextrose, flavor, glycerin, magnesium stearate, maltodextrin, mannitol, pregelatinized starch, saccharin sodium, sorbitol, sugar

PDP

Alumox

Antacid+Antigas

Lemon Flavor

Aluminum Hydroxide / Antacid

Magnesium Hydroxide / Antacid

Simethicone / Antigas

FOR FAST RELIEF OF:

Acid indigestion

Sour stomach

Heartburn

Gas

100 Chewable Tablets